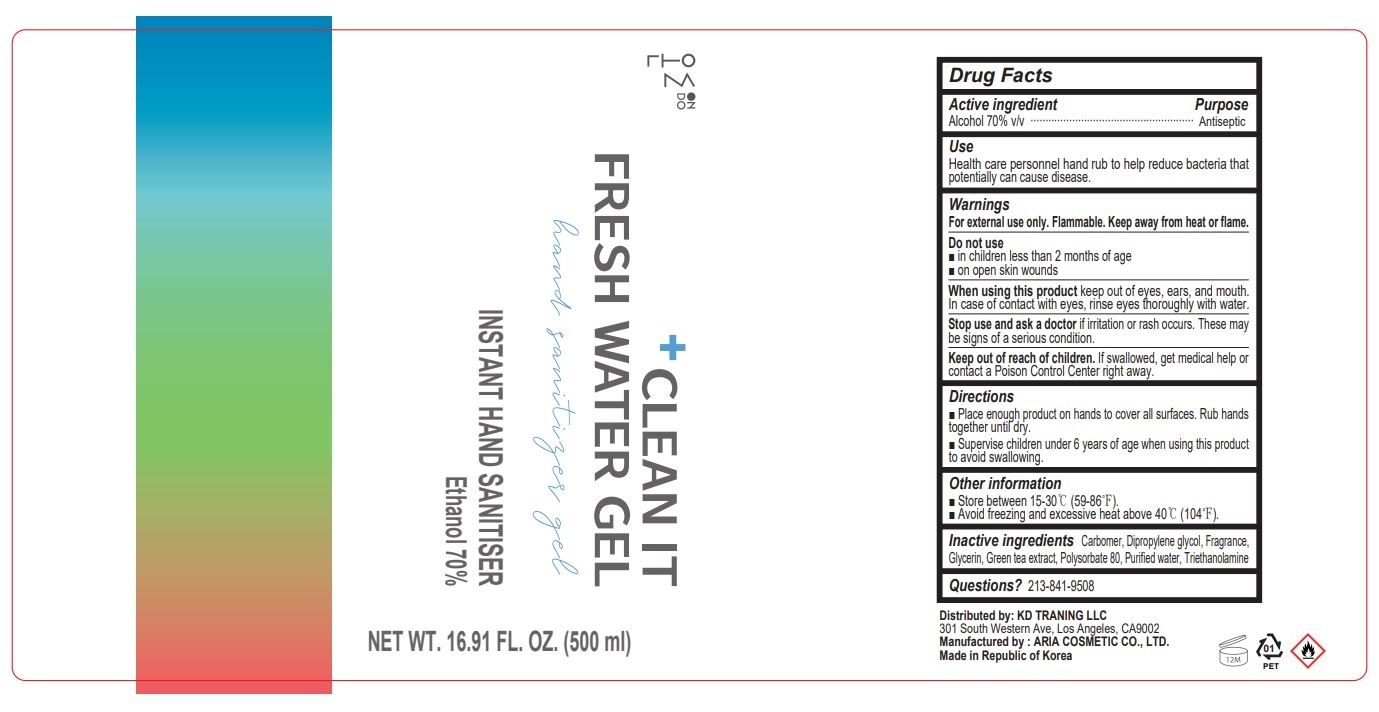 DRUG LABEL: CLEAN IT FRESH WATER GE L
NDC: 75229-101 | Form: GEL
Manufacturer: ARIA COSMETIC CO., LTD.
Category: otc | Type: HUMAN OTC DRUG LABEL
Date: 20200628

ACTIVE INGREDIENTS: ALCOHOL 350 mL/500 mL
INACTIVE INGREDIENTS: WATER; GLYCERIN; TROLAMINE; CARBOMER HOMOPOLYMER, UNSPECIFIED TYPE; POLYSORBATE 80; GREEN TEA LEAF; DIPROPYLENE GLYCOL

ACTIVE INGREDIENT

Alcohol

INACTIVE INGREDIENT

Carbomer, Dipropylene glycol, Fragrance, Glycerin, Green tea extract, Polysorbate 80, Purified water, Triethanolamine

PURPOSE

Antiseptic
Instant hand sanitizer to decrease bacteria on the skin

INDICATIONS AND USAGE

Health care personnel hand rub to help reduce bacteria that potentially can cause disease.

■ Place enough product on hands to cover all surfaces. Rub hands together until dry.
■ Supervise children under 6 years of age when using this product to avoid swallowing.

WARNINGS

For external use only. Flammable. Keep away from heat or flame.

DO NOT USE

■ in children less than 2 months of age
■ on open skin wounds

When using this product keep out of eyes, ears, and mouth. In case of contact with eyes, rinse eyes thoroughly with water.

Stop use and ask a doctor if irritation or rash occurs. These may be signs of a serious condition.

Keep out of reach of children. If swallowed, get medical help or contact a Poison Control Center right away.

STORAGE AND HANDLING

■ Store between 15-30℃ (59-86℉).
■ Avoid freezing and excessive heat above 40℃ (104℉).

DOSAGE AND ADMINISTRATION

Pump 1-2 times and rub it into your hand. For topical use only.